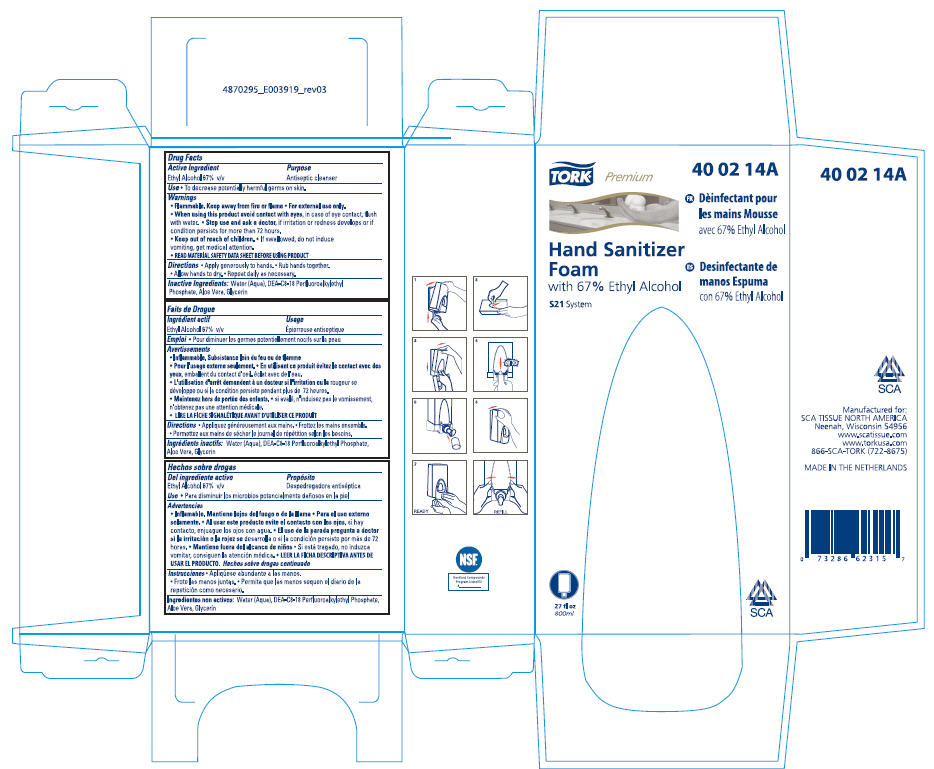 DRUG LABEL: Tork Premium Hand Sanitizer Foam
NDC: 49351-018 | Form: LIQUID
Manufacturer: SCA Tissue North America
Category: otc | Type: HUMAN OTC DRUG LABEL
Date: 20100427

ACTIVE INGREDIENTS: Alcohol 67 mL/100 mL
INACTIVE INGREDIENTS: Water; Aloe Vera Leaf; Glycerin

TORK®
Hand Sanitizer
Foam

Drug Facts

Active Ingredient

Ethyl Alcohol 67% v/v

Purpose

Antiseptic cleanser

Use

- To decrease potentially harmful germs on skin.

Warnings

- Flammable. Keep away from fire or flame
- For external use only.

- When using this product avoid contact with eyes, in case of eye contact, flush with water.

- Stop use and ask a doctor, if irritation or redness develops or if condition persists for more than 72 hours.

- Keep out of reach of children.
- If swallowed, do not induce vomiting, get medical attention.
- READ MATERIAL SAFETY DATA SHEET BEFORE USING PRODUCT

Directions

- Apply generously to hands.
- Rub hands together.
- Allow hands to dry.
- Repeat daily as necessary.

Inactive Ingredients

Water (Aqua), DEA-C8-18 Perfluoroalkylethyl Phosphate, Aloe Vera, Glycerin

Manufactured for:
SCA TISSUE NORTH AMERICA
Neenah, Wisconsin 54956
www.scatissue.com
www.torkusa.com
866-SCA-TORK (722-8675)

PRINCIPAL DISPLAY PANEL - 800ml Carton

TORK®
Premium
40 02 14A

Hand Sanitizer
Foam
with 67% Ethyl Alcohol

S21 System

27 fl oz
800ml

SCA